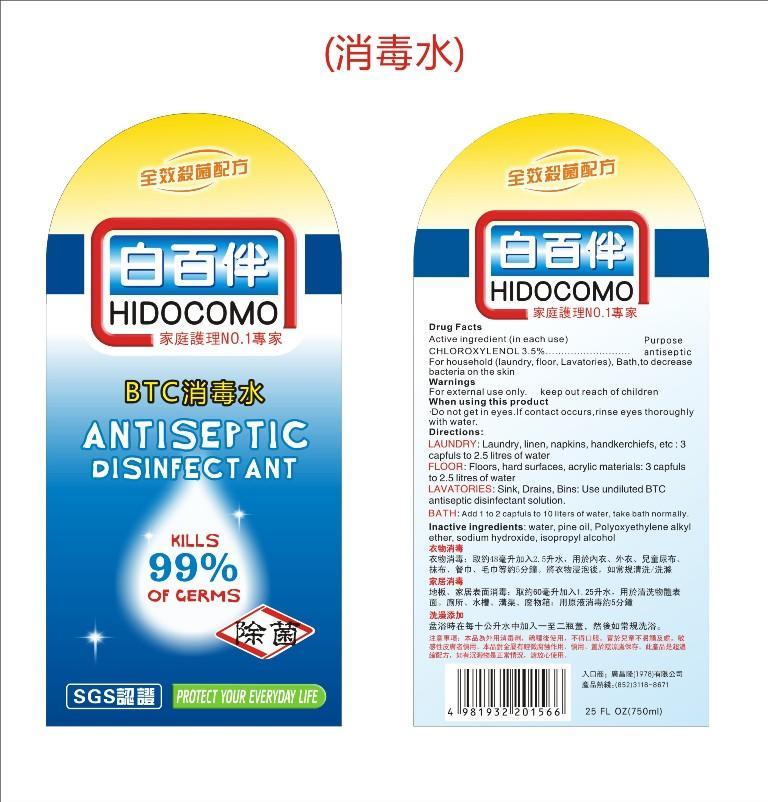 DRUG LABEL: Hidocomo Antiseptic Disinfectant
NDC: 54476-100 | Form: LIQUID
Manufacturer: Toma Biotechnology International Corporation-China Division
Category: otc | Type: HUMAN OTC DRUG LABEL
Date: 20130228

ACTIVE INGREDIENTS: CHLOROXYLENOL 3.5 g/100 mL
INACTIVE INGREDIENTS: Propyl alcohol; .ALPHA.-TERPINEOL; C12-15 ALCOHOLS; Sodium Hydroxide; Water; Caramel; C.I. FOOD YELLOW 3 (FREE ACID)

Hidocomo Antiseptic Disinfectant

Active ingredient

CHLOROXYLENOL 3.5%

Purpose

antiseptic

Use

For household (laundry,floor,Lavatories),bath,to decrease bacteria on the skin.

Warnings

For external use only. Do not get in eyes,If contact occurs,rinse eyes thoroughly with water

Keep out of reach of children

Directions

Laundry:laundry,linen,napkins,handkerchiefs,etc:3 capfuls to 2.5 litres of water. Floor:Floors,hard surfaces,acrylic materials: 3 capfuls to 2.5 litres of water. Lavatories:Sink,Drains,Bins:Use undiluted BTC antiseptic disinfectant solution. Bath:Add 1 to 2 capfuls to 10 liters of water,take bath normally

INACTIVE INGREDIENT

water,pine oil,polyoxyethylene alkylether,sodium hydroxide,isopropyl alcohol